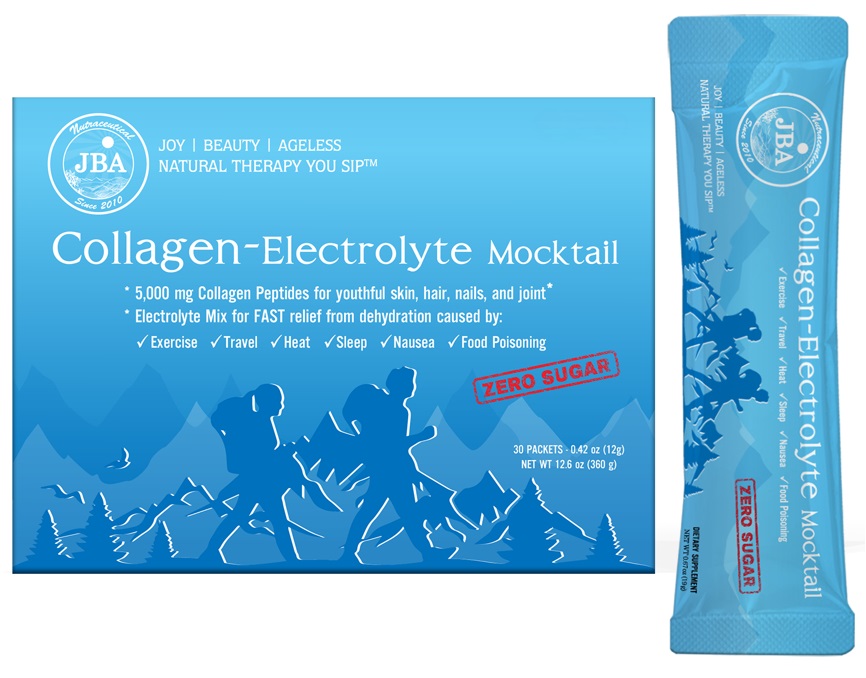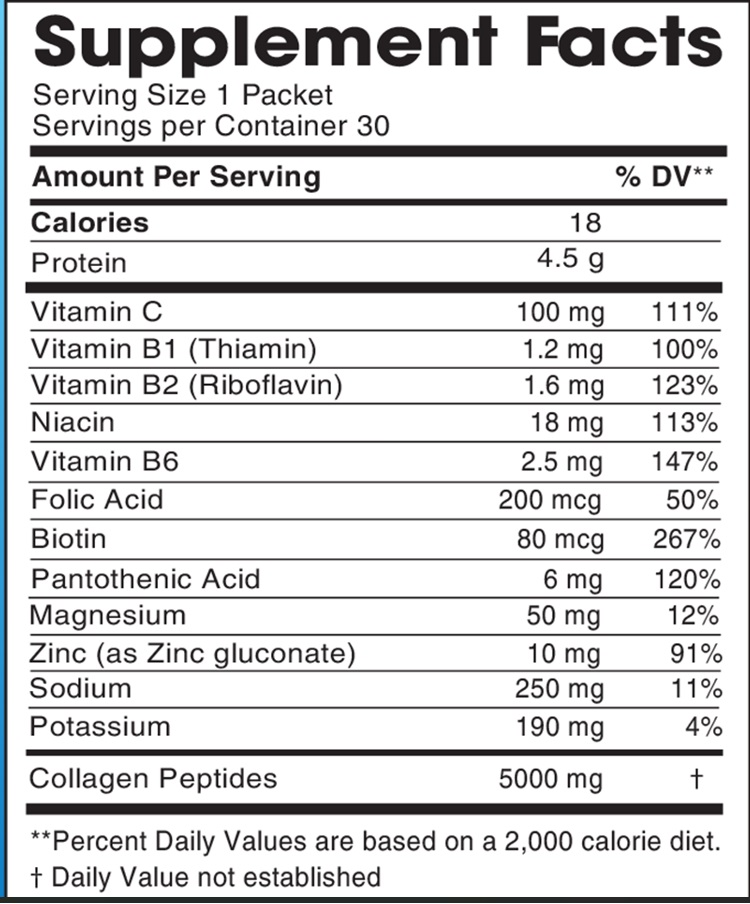 DRUG LABEL: JBA Collagen-Electrolyte Mocktail
NDC: 13411-848 | Form: POWDER
Manufacturer: Advanced Pharmaceutical Services, Inc. Dba Affordable Quality Pharmaceuticals
Category: otc | Type: HUMAN OTC DRUG LABEL
Date: 20250331

ACTIVE INGREDIENTS: ASCORBIC ACID 100 mg/12 g; THIAMINE 1.2 mg/12 g; RIBOFLAVIN 1.6 mg/12 g; NIACIN 18 mg/12 g; PYRIDOXINE 2.5 mg/12 g; FOLIC ACID 200 ug/12 g; BIOTIN 80 ug/12 g; PANTOTHENIC ACID 6 mg/12 g; MAGNESIUM 50 mg/12 g; ZINC 10 mg/12 g; SODIUM 250 mg/12 g; POTASSIUM 190 mg/12 g
INACTIVE INGREDIENTS: ANHYDROUS CITRIC ACID; POVIDONE K30; MALTODEXTRIN; MANNITOL; STEVIA REBAUDIUNA LEAF; SUCRALOSE

Identity

Dietary supplement

Warnings

BEFORE USING this dietary supplement ask your doctor if you

- Are considering using this product as part of a cholesterol lowering program
- Are using medication to control your blood sugar levels
- Have recently experienced abdominal pain, nausea, vomiting or a sudden change in bowel habits persisting for two weeks.

Warning:
Bulk forming fibers like psyllium husk may affect how well medicines work. Take this product at least 2 hours before or after medicines.

Direction

Your morning self-care ritual:
Pour one packet into your favorite glass
Add 8-12 oz water to taste
Drink promptly and enjoy!

Safe handling warning

Store in a cool, dry place

HEALTH CLAIM

JBA® Collagen-Electrolyte Mocktail

5,000 mg Collagen Peptides for youthful skin, hair, nail, and joint*
Electrolyte Mix for FAST relief from dehydration caused by:

- Exercise
- Travel
- Heat
- Sleep
- Nausea
- Food Poisoning

Collagen-Electrolyte Mocktail
Collagen Meets Hydration – Enjoy Healing in every cup ™

Collagen

- Strengthen hair, skin, and nails*
- Supporting muscles and joint health*
- Supporting control blood sugar*
- Supporting immune health*

Electrolyte

- Support rapid hydration and replenish electrolytes*
- Promotes relaxation and rest quality*
- Help ease feeling of stress*

With 5,000 mg collagen peptides and 111% Daily Recommended Value of Vitamin C, acting as an antioxidant to help replenish collagen levels for firmer, plumper, younger-looking skin and stronger, healthier hair, nails and joints.

* These statements have not been evaluated by the Food & Drug Administration. This product is not intended to diagnose, treat, cure, or prevent any disease.